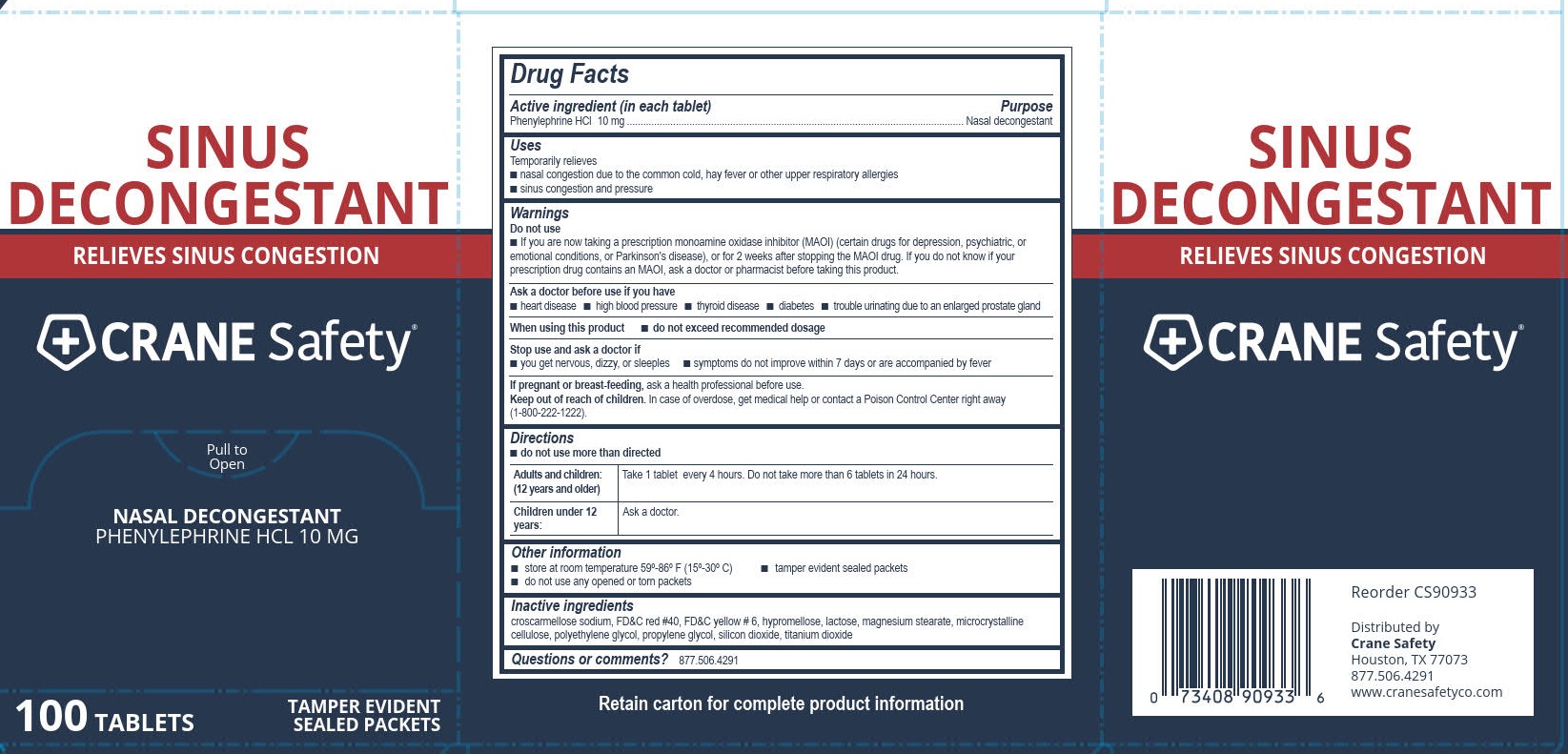 DRUG LABEL: Crane Safety Sinus Decongestant
NDC: 73408-990 | Form: TABLET, FILM COATED
Manufacturer: Crane Safety LLC
Category: otc | Type: HUMAN OTC DRUG LABEL
Date: 20250908

ACTIVE INGREDIENTS: PHENYLEPHRINE HYDROCHLORIDE 10 mg/1 1
INACTIVE INGREDIENTS: MAGNESIUM STEARATE; PROPYLENE GLYCOL; CROSCARMELLOSE SODIUM; POLYETHYLENE GLYCOL, UNSPECIFIED; FD&C RED NO. 40; FD&C YELLOW NO. 6; HYPROMELLOSE, UNSPECIFIED; LACTOSE, UNSPECIFIED FORM; CELLULOSE, MICROCRYSTALLINE; TITANIUM DIOXIDE; SILICON DIOXIDE

Crane Safety Sinus Decongestant

Active ingredient (in each tablet)

Phenylephrine HCl 10 mg

Purpose

Nasal decongestant

Uses

Temporarily relieves

■ nasal congestion due to the common cold, hay fever or other upper respiratory allergies

■ sinus congestion and pressure

Do not use

- if you are now taking a prescription monoamine oxidase inhibitor (MAOI) (certain drugs for depression, psychiatric, or emotional conditions, or Parkinson's disease), or for 2 weeks after stopping the MAOI drug. If you do not know if your prescription drug contains an MAOI, ask a doctor or pharmacist before taking this product.

Ask a doctor before use if you have

- heart disease
- high blood pressure
- thyroid disease
- diabetes
- trouble urinating due to an enlarged prostate gland

When using this product

- do not exceed recommended dosage

Stop use and ask a doctor if

- you get nervous, dizzy, or sleepless
- symptoms do not improve within 7 days or are accompanied by fever

PREGNANCY OR BREAST FEEDING

If pregnant or breast feeding, ask a health professional before use.

Keep out of reach of children.

In case of overdose, get medical help or contact a Poison Control Center right away (1-800-222-1222).

Directions

- do not use more than directed

Adults and children: (12 years and older) Take 1 tablet every 4 hours. Do not take more than 6 tablets in 24 hours.

Children under 12 years: Ask a doctor

Other information

- store at room temperature 59º-86º F (15º-30º C)
- tamper evident sealed packets
- do not use any opened or torn packets

Inactive ingredients

croscarmellose sodium, FD&C red #40, FD&C yellow # 6, hypromellose, lactose, magnesium stearate, microcrystalline cellulose, polyethylene glycol, propylene glycol, silicon dioxide, titanium dioxide

Questions or comments?

877.506.4291

Crane Safety Sinus Decongestant Label

Sinus Decongestant

Relieves Sinus Congestion

CRANE Safety®

Pull to Open

Nasal Decongestant

Phenylephrine HCl 10MG

100 Tablets

Tamper Evident

Sealed Packets